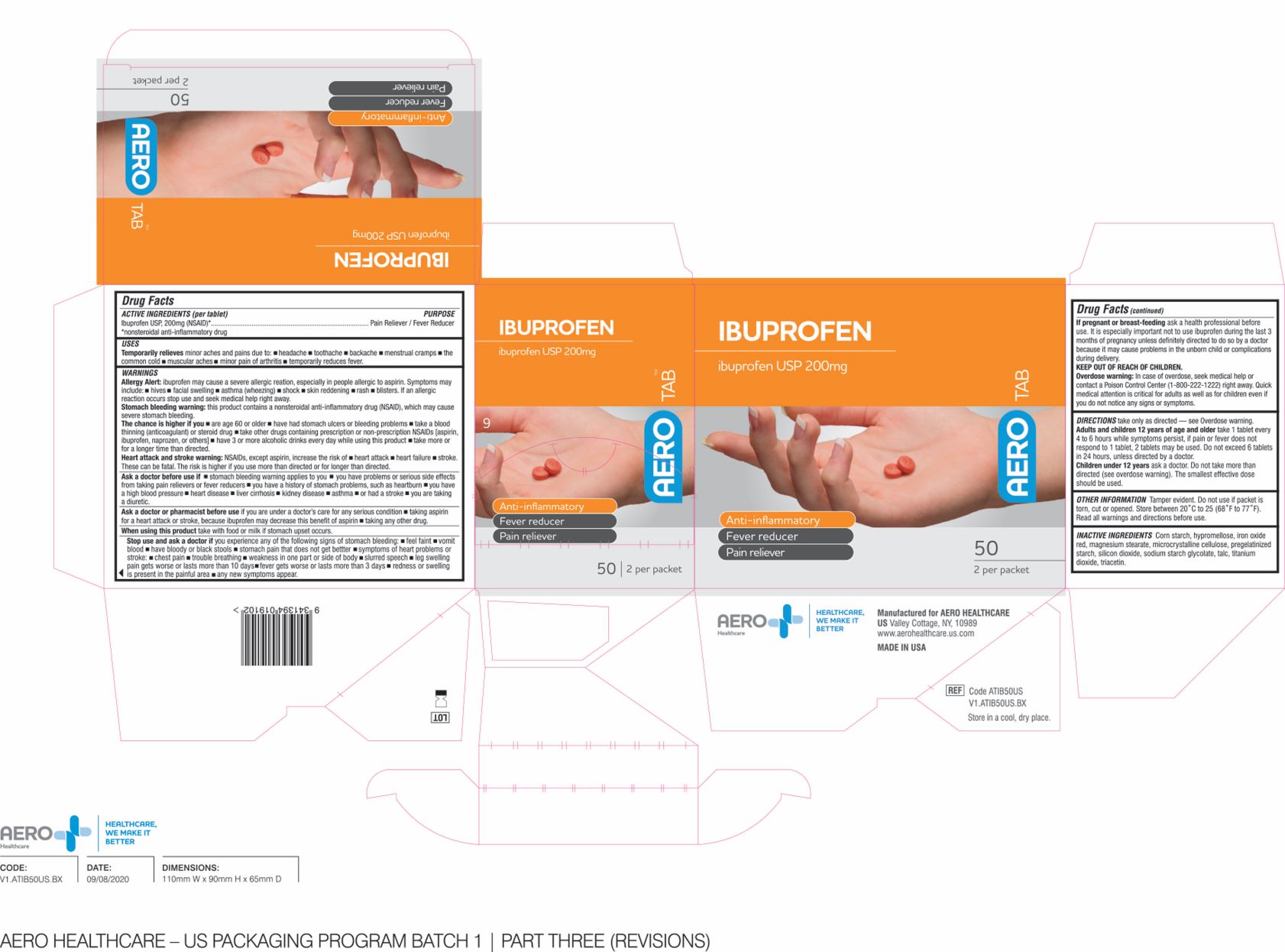 DRUG LABEL: AeroTab Ibuprofen
NDC: 55305-133 | Form: TABLET, COATED
Manufacturer: Aero Healthcare
Category: otc | Type: HUMAN OTC DRUG LABEL
Date: 20250226

ACTIVE INGREDIENTS: IBUPROFEN 200 mg/1000 mg
INACTIVE INGREDIENTS: STARCH, CORN; TALC; CROSCARMELLOSE SODIUM; MAGNESIUM STEARATE; POLYETHYLENE GLYCOL 1000; POLYVINYL ALCOHOL (100000 MW); MICROCRYSTALLINE CELLULOSE; TITANIUM DIOXIDE; SILICON DIOXIDE

AeroTab Ibuprofen Tablets

ACTIVE INGREDIENT

Drug Facts

Active Ingredient (in each tablet)
Ibuprofen 200 mg (NSAID)*

PURPOSE

Ibuprofen 200 mg (NSAID)*.............Pain Reliever Fever Reducer

*nonsteroidal anti-inflammatory drug

INDICATIONS & USAGE

Uses:
Temporarily Relieves minor aches and pains
due to:
• Headache, toothaches, backache, menstrual cramps,
the common cold,
• muscular aches, minor pain of arthritis
Temporarily reduces fever

WARNINGS

Allergy Alert: Ibuprofen may cause a severe allergic reaction, especially in people allergic to aspirin.
Symptoms may include:
• hives, facial swelling, asthma (wheezing), shock,
skin reddening, rash, blisters. If an allergic reaction occurs stop use an dseek medical help right away.

Stomach bleeding warning: This product contains a nonsteroidal anti-inflammatory drug (NSAID), which may cause severe stomach bleeding.
The chance is higher if you:
• are age 60 or older
• have had stomach ulcers or bleeding problems
• take a blood thinning (anticoagulant) or steroid
drug
• take other drugs containing prescription NSAIDs
(aspirin, ibuprofen, naproxen, or others)
• have 3 or more alcoholic drinks every day while
using this product
• take more or for a longer time than directed

Heart attack and stroke warning: NSAIDs, except aspirin, increase the risk of heart attack, heart failure, stroke. These can be fatal. The risk is higher if you use more than directed or for longer than directed.

Ask a doctor before use if

- stomach bleeding warning applies to you
- you have problems or serious side effects from taking pain relievers or frever reducers
- you have a history of stomach problems, such as heartburn
- you have high blood pressure, heart disease, liver cirrhosis, kidney disease, asthma, had a stroke, you are taking a diuretic

Ask a doctor or pharmacist before use if

- you are under a doctor's care for any serious condition
- Taking aspirin for a heart attack or stroke, because ibuprofen may decrease this benefit of asprin
- taking any other drug

When using this product take with food or milk if stomach upset occurs

Stop use and ask a doctor if you experience any of the following signs of stomach bleeding:

- feel faint
- vomit
- blood
- have bloody or black stools
- stomach pain that does not get better
- symptoms of heart problems or stroke
- chest pain
- trouble breathing
- weakness in one part or side of body
- slurred speech
- leg swelling
- pain gets worse or last more than 10 days
- fever gets worse or last more than 3 days
- redness or swelling is present in the painful area
- any new symptoms appear

If pregnant or breast-feeding, ask a health professional before use. It is especially important not to use ibuprofen during the last 3 months of pregnancy unless definitely directed to do so by a doctor because it may cause problems in the unborn child or complications during delivery.

KEEP OUT OF REACH OF CHILDREN

Overdose warning: In case of overdose, seek medical help or contact a Poison Control Center (1-800-222-1222) right away.

Quick medical attention is critical for adults as well as for children even if you do not notice any signs or symptoms.

DOSAGE & ADMINISTRATION

Directions: take only as directed - see Overdose warning.

Adults and children 12 years of age and older take 1 tablet every 4 to 6 hours while symptoms persist, if pain or fever does not respond to 1 tablet, 2 tablets may be used. Do not exceed 6 tablets in 24 hoiurs, unless directed by a doctor.

Children under 12 years ask a doctor. Do not take more than directed (see overdose warning). The smallest effective dose should be used.

OTHER INFORMATION

Tamper evident. Do not use if packet is torn, cut or opened. Store between 20C to 25C (68F to 77F). Read all warnings and directions before use

INACTIVE INGREDIENTS

corn starch, hypromellose, red iron oxide, magnesium stearate, microcrystalline cellulose, pregelatinized starch,silicon dioxide, sodium starch glycolate, talc, titanium dioxide, triacetin

Ibuprofen Package

AeroTab

Ibuprofen USP 200mg

Anti-inflammatory

Fever reducer

Pain reliever

250

2 per packet